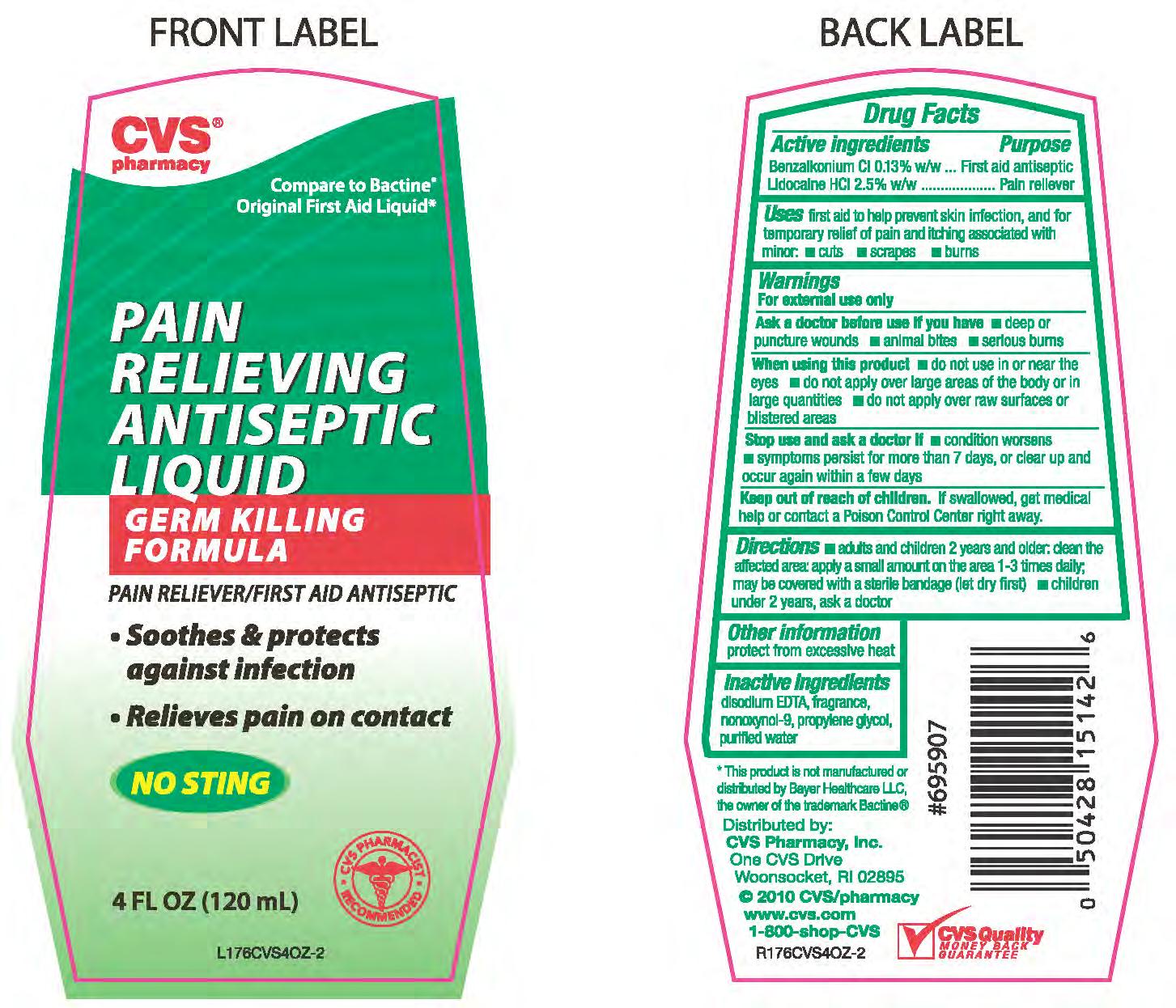 DRUG LABEL: BENZALKONIUM CHLORIDE AND LIDOCAINE HYDROCHLORIDE
NDC: 59779-255 | Form: LIQUID
Manufacturer: CVS Pharmacy
Category: otc | Type: HUMAN OTC DRUG LABEL
Date: 20100708

ACTIVE INGREDIENTS: BENZALKONIUM CHLORIDE 26 mg/1 mL; LIDOCAINE HYDROCHLORIDE 25 mg/1 mL
INACTIVE INGREDIENTS: WATER; PROPYLENE GLYCOL; EDETATE DISODIUM; NONOXYNOL-9

drug facts

Active ingredient Purpose
Benzalkonium Cl 0.13% w/w...............................Antiseptic
lidocaine HCl 2.5% w/w......................................Pain reliever

Active ingredient Purpose
Benzalkonium Cl 0.13% w/w...............................Antiseptic
lidocaine HCl 2.5% w/w......................................Pain reliever
Uses first aid to help prevent skin infection, and for temporary relief of pain
and itching associated with minor - cuts - scrapes - burns

Keep out of reach of children. If swallowed, get medical help
or contact a Poison Control Center right away.

INDICATIONS AND USAGE

Directions - adults and children 2 years and older; clean the affected area; apply a
small amount on the area 1-3 times daily; may be covered with a sterile bandage (let dry first)
- children under 2 years, ask a doctor.

Uses first aid to help prevent skin infection, and for temporary relief of pain
and itching associated with minor - cuts - scrapes - burns

Warnings
For external use only.
Ask a doctor before use if you have - deep or puncture wounds
- animal bites - serious burns
When using this product - do not use in or near the eyes - do not
apply over large areas of the body or in large quantities - do not apply
over raw surfaces or blistered areas.
Stop use and ask a doctor if - condition worsens - symptoms
persist for more than 7 days, or clear up and occur again within a few days
Keep out of reach of children. If swallowed, get medical
help or contact a Poison Control Center right awayImmediately.

DOSAGE AND ADMINISTRATION

Directions - adults and children 2 years and older; clean the affected area; apply a
small amount on the area 1-3 times daily; may be covered with a sterile bandage
(let dry first)- children under 2 years, ask a doctor.
Other Information protect from excessive heat

INACTIVE INGREDIENT

Inactive Ingredients disodium EDTA, fragrance, nonoxynol-9, propylene glycol,
purified water